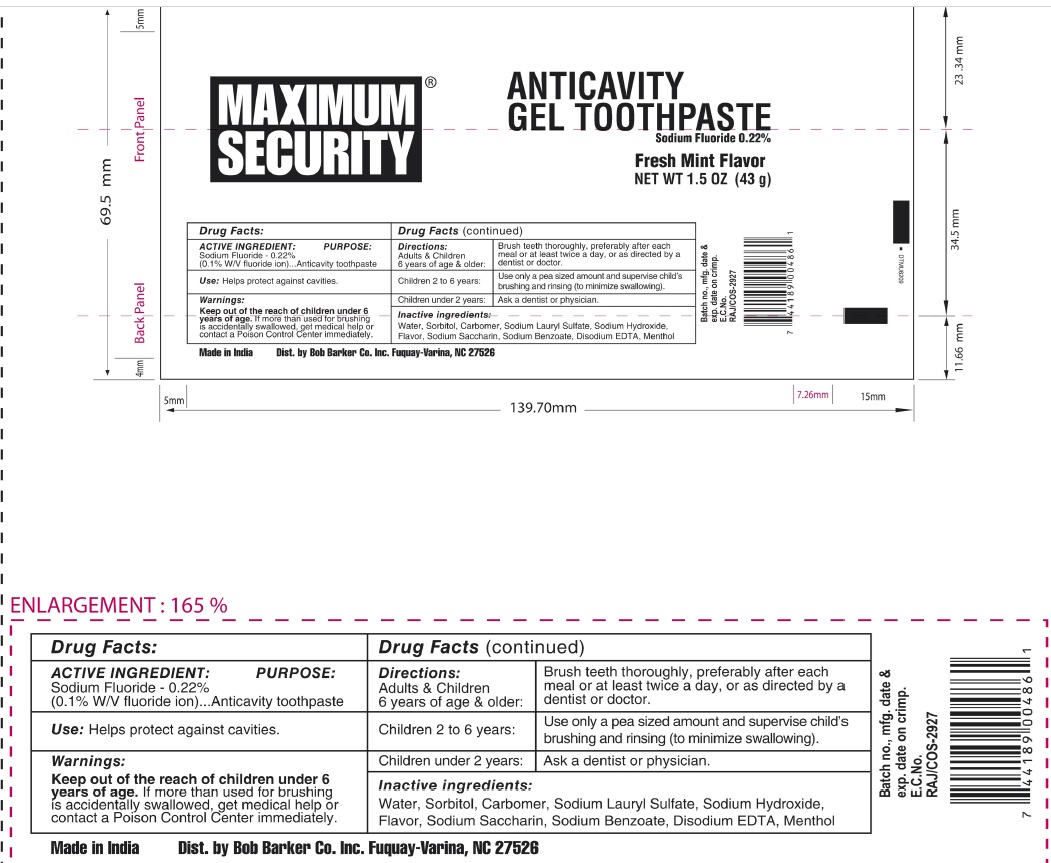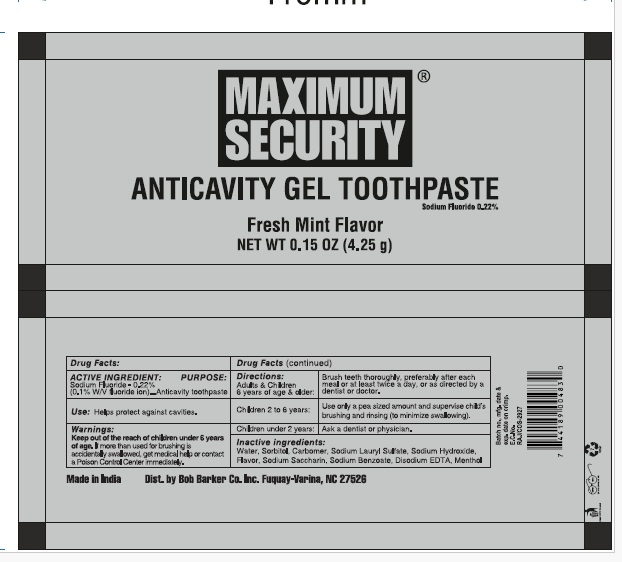 DRUG LABEL: Maximum Security Anticavity Gel fresh mint flavor
NDC: 85891-008 | Form: PASTE
Manufacturer: SPARROW LIFE CARE PRIVATE LIMITED
Category: otc | Type: HUMAN OTC DRUG LABEL
Date: 20250825

ACTIVE INGREDIENTS: SODIUM FLUORIDE 0.1 g/100 g
INACTIVE INGREDIENTS: WATER; SORBITOL; CARBOMER HOMOPOLYMER TYPE C (ALLYL PENTAERYTHRITOL CROSSLINKED); SODIUM LAURYL SULFATE; SODIUM HYDROXIDE; SODIUM SACCHARIN; SODIUM BENZOATE; EDETATE DISODIUM; MENTHOL

Active Ingredient

Sodium Fluoride 0.22 % (0.1 % W/V Fluoride Ion)

Purpose

Anticavity Toothpaste

Uses

• Help Protect against cavities

Warnings

• Keep out of the reach of children under 6 years of age. If more than used for brushing is accidentally swallowed. Get medical help or contact a poison control center immediately

Directions

Adults & children 6 years of age & older: | Brush teeth thoroughly, Preferably after each meal of at least twice a day, or as directed by a dentist or doctor
Children 2 to 6 years | Use only pea sized amount and supervise child’s brushing and rinsing (to minimize swallowing).
Children under 2 years | Ask a dentist or physician

Inactive ingredients

Water, Sorbitol, Carbomer, Sodium Lauryl Sulfate, Sodium Hydroxide, Flavor, Sodium saccharin, Sodium Benzoate, Disodium EDTA, Menthol